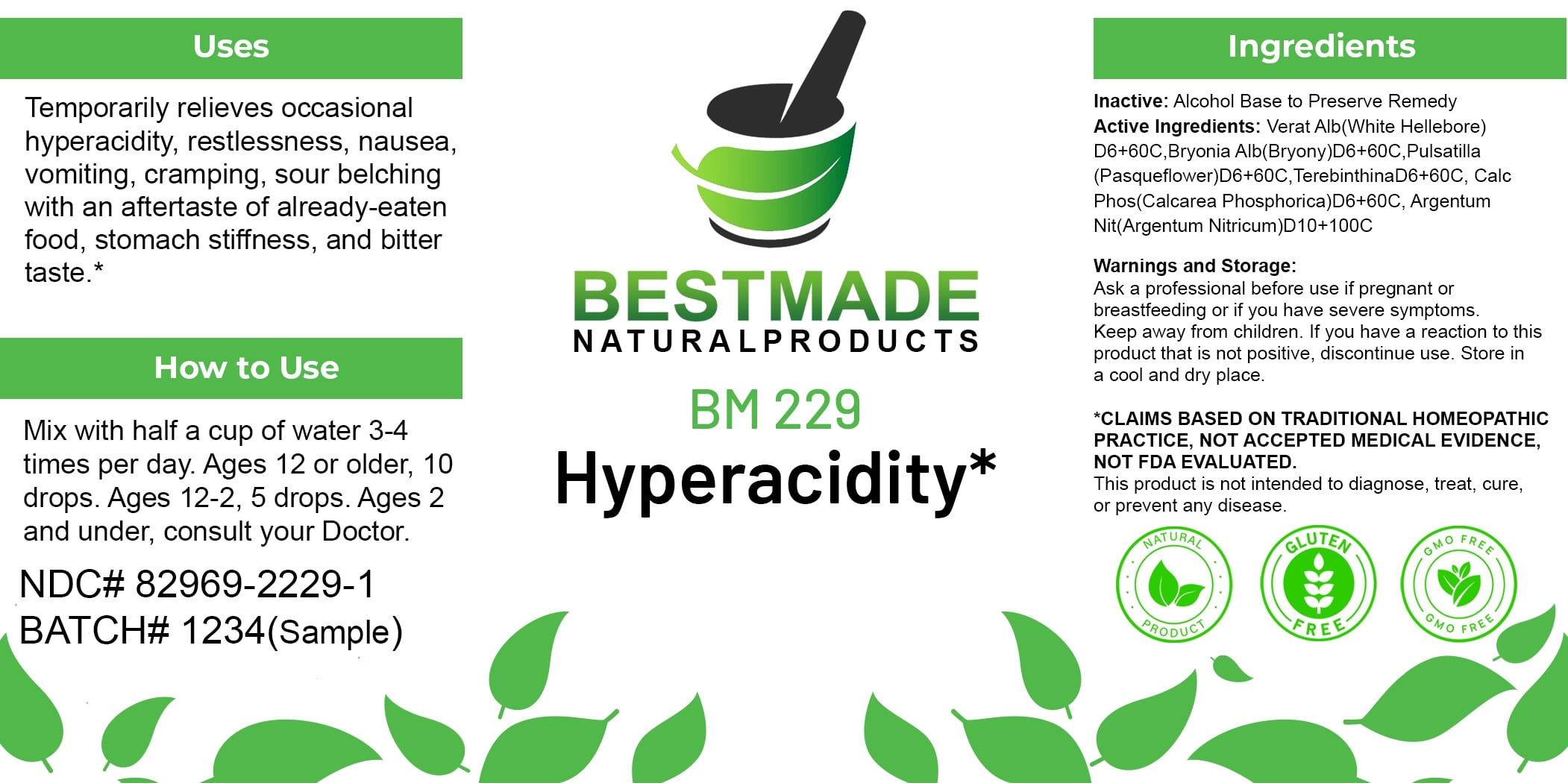 DRUG LABEL: Bestmade Natural Products BM229
NDC: 82969-2229 | Form: LIQUID
Manufacturer: Bestmade Natural Products
Category: homeopathic | Type: HUMAN OTC DRUG LABEL
Date: 20250304

ACTIVE INGREDIENTS: SILVER NITRATE 60 [hp_C]/60 [hp_C]; BRYONIA ALBA ROOT 60 [hp_C]/60 [hp_C]; TRIBASIC CALCIUM PHOSPHATE 60 [hp_C]/60 [hp_C]; PULSATILLA VULGARIS 60 [hp_C]/60 [hp_C]; TURPENTINE OIL 60 [hp_C]/60 [hp_C]; VERATRUM ALBUM ROOT 60 [hp_C]/60 [hp_C]
INACTIVE INGREDIENTS: ALCOHOL 60 [hp_C]/60 [hp_C]

BM229

DOSAGE AND ADMINISTRATION

How to Use

Mix with half a cup of water 3-4 times per day. Ages 12 or older, 10 drops. Ages 12-2, 5 drops. Ages 2 and under, consult your Doctor.

Uses

Temporarily relieves occasional hyperacidity, restlessness, nausea, vomiting, cramping, sour belching with an aftertaste of already-eaten food, stomach stiffness, and bitter taste.*

*CLAIMS BASED ON TRADITIONAL HOMEOPATHIC PRACTICE, NOT ACCEPTED MEDICAL EVIDENCE. NOT FDA EVALUATED.

This product is not intended to diagnose, treat, cure, or prevent any disease.

INACTIVE INGREDIENT

Ingredients

Inactive: Alcohol Base to Preserve Remedy

ACTIVE INGREDIENT

Active Ingredients: Verat Alb(White Hellebore) D6+60C, Bryonia Alb(Bryony)D6+60C, Pulsatilla (Pasqueflower)D6+60C, TerebinthinaD6+60C, Calc Phos(Calcarea Phosphorica)D6+60C, Argentum Nit(Argentum Nitricum)D10+100C

KEEP OUT OF REACH OF CHILDREN

Warnings and Storage:

Ask a professional before use if pregnant or breastfeeding or if you have severe symptoms. Keep away from children. If you have a reaction to this product that is not positive, discontinue use. Store in a cool and dry place.

Warnings and Storage:

Ask a professional before use if pregnant or breastfeeding or if you have severe symptoms. Keep away from children. If you have a reaction to this product that is not positive, discontinue use. Store in a cool and dry place.

*CLAIMS BASED ON TRADITIONAL HOMEOPATHIC PRACTICE, NOT ACCEPTED MEDICAL EVIDENCE. NOT FDA EVALUATED.

This product is not intended to diagnose, treat, cure, or prevent any disease.

Uses

Temporarily relieves occasional hyperacidity, restlessness, nausea, vomiting, cramping, sour belching with an aftertaste of already-eaten food, stomach stiffness, and bitter taste.*

*CLAIMS BASED ON TRADITIONAL HOMEOPATHIC PRACTICE, NOT ACCEPTED MEDICAL EVIDENCE. NOT FDA EVALUATED.

This product is not intended to diagnose, treat, cure, or prevent any disease.

Entire package label